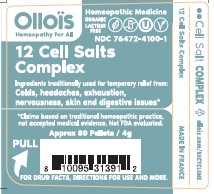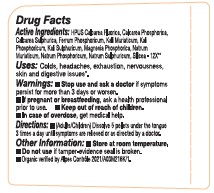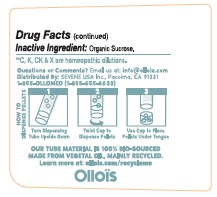 DRUG LABEL: 12 CELL SALTS COMPLEX
NDC: 76472-4100 | Form: PELLET
Manufacturer: SEVENE USA
Category: homeopathic | Type: HUMAN OTC DRUG LABEL
Date: 20250210

ACTIVE INGREDIENTS: DIBASIC POTASSIUM PHOSPHATE 6 [hp_X]/1 1; SILICON DIOXIDE 6 [hp_X]/1 1; CALCIUM SULFATE ANHYDROUS 6 [hp_X]/1 1; FERROSOFERRIC PHOSPHATE 6 [hp_X]/1 1; SODIUM PHOSPHATE, DIBASIC, HEPTAHYDRATE 6 [hp_X]/1 1; CALCIUM FLUORIDE 6 [hp_X]/1 1; POTASSIUM CHLORIDE 6 [hp_X]/1 1; MAGNESIUM PHOSPHATE, DIBASIC TRIHYDRATE 6 [hp_X]/1 1; SODIUM SULFATE 6 [hp_X]/1 1; SODIUM CHLORIDE 6 [hp_X]/1 1; TRIBASIC CALCIUM PHOSPHATE 6 [hp_X]/1 1; POTASSIUM SULFATE 6 [hp_X]/1 1
INACTIVE INGREDIENTS: SUCROSE

Sevene USA (as PLD) - 12 CELL SALTS COMPLEX (76472-4100)

ACTIVE INGREDIENTS:

HPUS CALCAREA FLUORICA, CALCAREA PHOSPHORICA, CALCAREA SULPHURICA, FERRUM PHOSPHORICUM, KALI MURIATICUM, KALI PHOSPHORICUM, KALI SULPHURICUM, MAGNESIA PHOSPHORICA, NATRUM MURIATICUM, NATRUM PHOSPHORICUM, NATRUM SULPHURICUM, SILICEA - 6X**

**C, K, CK & X are homeopathic dilutions.

TRADITIONALLY USED FOR TEMPORARY RELIEF FROM:

COLDS, HEADACHES, EXHAUSTION, NERVOUSNESS, SKIN AND DIGESTIVE ISSUES*

*Claims based on traditional homeopathic practice, not accepted medical evidence. Not FDA evaluated

DIRECTIONS:

- (adults/children) Dissolve 5 pellets under the tongue 3 times a day until symptoms are relieved or as directed by a physician.

USES:

COLDS, HEADACHES, EXHAUSTION, NERVOUSNESS, SKIN AND DIGESTIVE ISSUES**

**C, K, CK & X ARE HOMEOPATHIC DILUTIONS.

WARNINGS:

- Stop use and ask a doctor if symptoms persist for more than 3 days or worsen.

PREGNANCY OR BREAST FEEDING

- If pregnant or breast-feeding, ask a health professional prior to use.

- Keep out of reach of children.
- In case of overdose, get medical help.

OTHER INFORMATION:

- Store at room temperature.
- Do not use if tamper-evidence seal is broken.
- Organic verified by Alpes Contrôle 2021/A03M216K/1.

INACTIVE INGREDIENT:

Organic Sucrose.

QUESTIONS OR COMMENTS?

Email us at: info@ollois.com